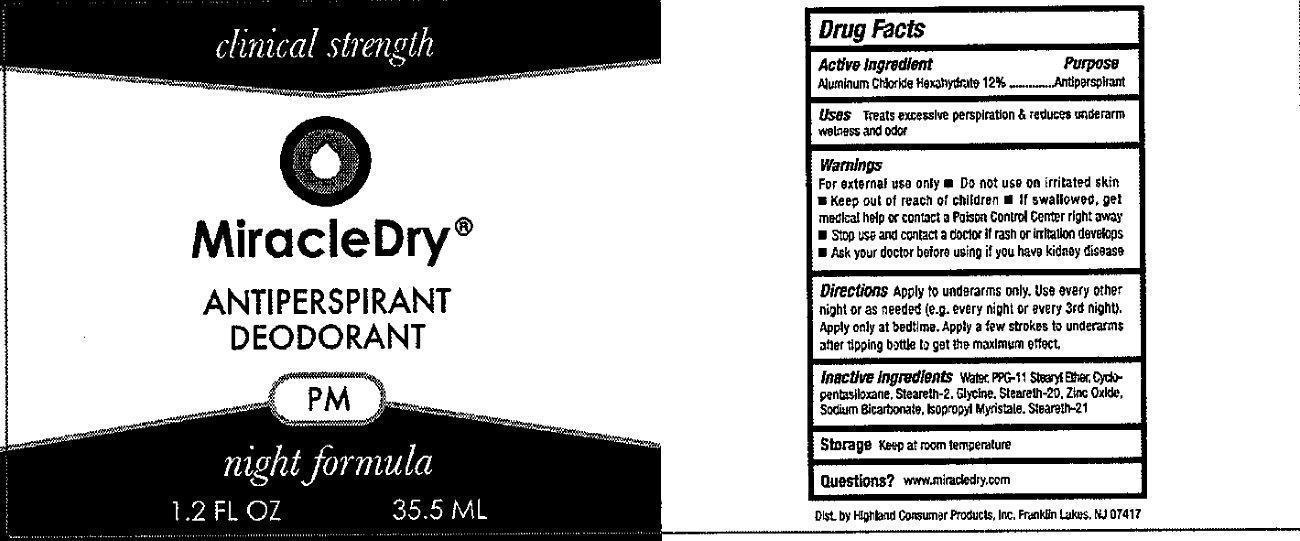 DRUG LABEL: Clinical Strength MiracleDry Antiperspirant Deodorant  PM

NDC: 53897-001 | Form: LIQUID
Manufacturer: Highland Consumer Products
Category: otc | Type: HUMAN OTC DRUG LABEL
Date: 20231212

ACTIVE INGREDIENTS: ALUMINUM CHLORIDE 12 mg/1 mL
INACTIVE INGREDIENTS: WATER; PPG-11 STEARYL ETHER; CYCLOMETHICONE 5; STEARETH-2; GLYCINE; STEARETH-20; ZINC OXIDE; SODIUM BICARBONATE; ISOPROPYL MYRISTATE; STEARETH-21

Clinical Strength MiracleDry Antiperspirant Deodorant PM

Active Ingredient

Aluminum Chloride Hexahydrate 12%

PURPOSE

Antiperspirant

Uses

Treats excessive perspiration and reduces underarm wetness and odor.

Warnings

For external use only

Do not use

on irritated skin.

Keep out of reach of children

If swallowed, get medical help or contact a Poison Control Center right away

Stop use and contact a doctor

if rash or irritation develops

Ask your doctor

before using if you have kidney disease

Directions

Apply to underarms only. Use every other night or as needed (e.g. every night or every 3rd nights). Apply only at bedtime. Apply few strokes to underarms after tipping bottle to get maximum effect.

Inactive Ingredients

Water, PPG-11 Stearyl Ether, Cyclopentasiloxane, Steareth-2, Glycine, Steareth-20, Zinc Oxide, Sodium Bicarbonate, Isopropyl Myristate, Steareth-21

Storage

Keep at room temperature

Questions?

www.miracledry.com

PACKAGE LABEL

clinical strength Miracle Dry ANTIPERSPIRANT DEODORANT PM NIGHT formula 1.2 FL OZ 35.5 ML